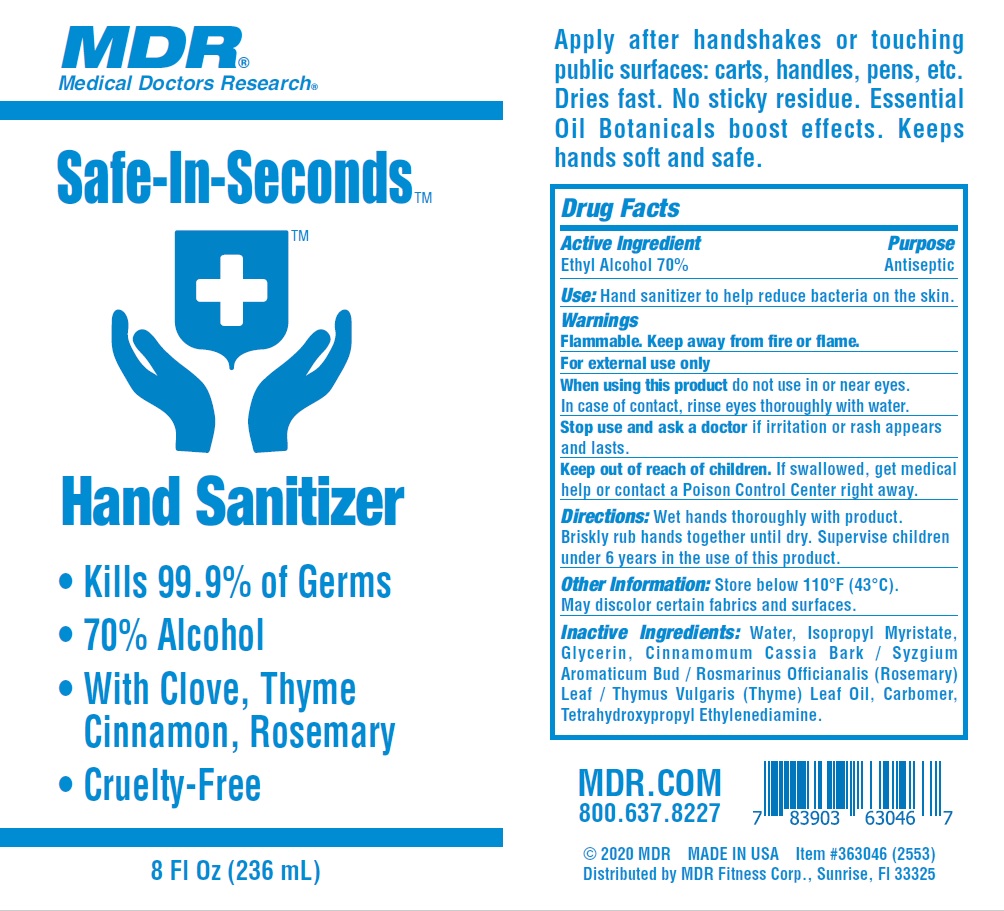 DRUG LABEL: MDR Safe-In-Seconds Hand Sanitizer
NDC: 64483-010 | Form: GEL
Manufacturer: Clientele, Inc.
Category: otc | Type: HUMAN OTC DRUG LABEL
Date: 20201028

ACTIVE INGREDIENTS: ALCOHOL 70 mL/100 mL
INACTIVE INGREDIENTS: GLYCERIN; CHINESE CINNAMON; SYZYGIUM AROMATICUM WHOLE; ROSEMARY; THYME OIL; CARBOMER HOMOPOLYMER, UNSPECIFIED TYPE; WATER; EDETOL; ISOPROPYL MYRISTATE

MDR Safe-In-Seconds Hand Sanitizer

Active Ingredient

Ethyl Alcohol 70%

Purpose

Antiseptic

Use

Hand sanitizer to help reduce bacteria on the skin.

Warnings

Flammable. Keep away from heat or flame.

For external use only

When using this product

do not use in or near eyes. In case of contact, rinse eyes thoroughly with water.

Stop use and ask a doctor

if irritation or rash appears and lasts.

Keep out of reach of children.

If swallowed, get medical help or contact a Poison Control Center right away.

Directions

Wet hands thoroughly with product. Briskly rub hands together until dry. Supervise children under 6 years in the use of this product.

Other Information

Store below 110F (43C). May discolor certain fabrics and surfaces.

Inactive Ingredients

Water, Isopropyl Myristate, Glycerin, Cinnamomum Cassia Bark/Syzgium Aromaticum Bud/Rosmarinus Officianalis (Rosemary) Leaf/Thymus Vulgaris (Thyme) Leaf Oil, Carbomer, Tetrahydroxypropyl Ethylenediamine.

Company Information

MDR.COM

800.637.8227

Distributed by MDR Fitness Corp., Sunrise, Fl 33325

Product Packaging - 236 mL

MDR

Medical Doctors Research

Safe-In-Seconds

Hand Sanitizer

- Kills 99.9% of Germs
- 70% Alcohol
- With Clove, Thyme, Cinnamon, Rosemary
- Cruelty-Free

8 Fl Oz (236 mL)